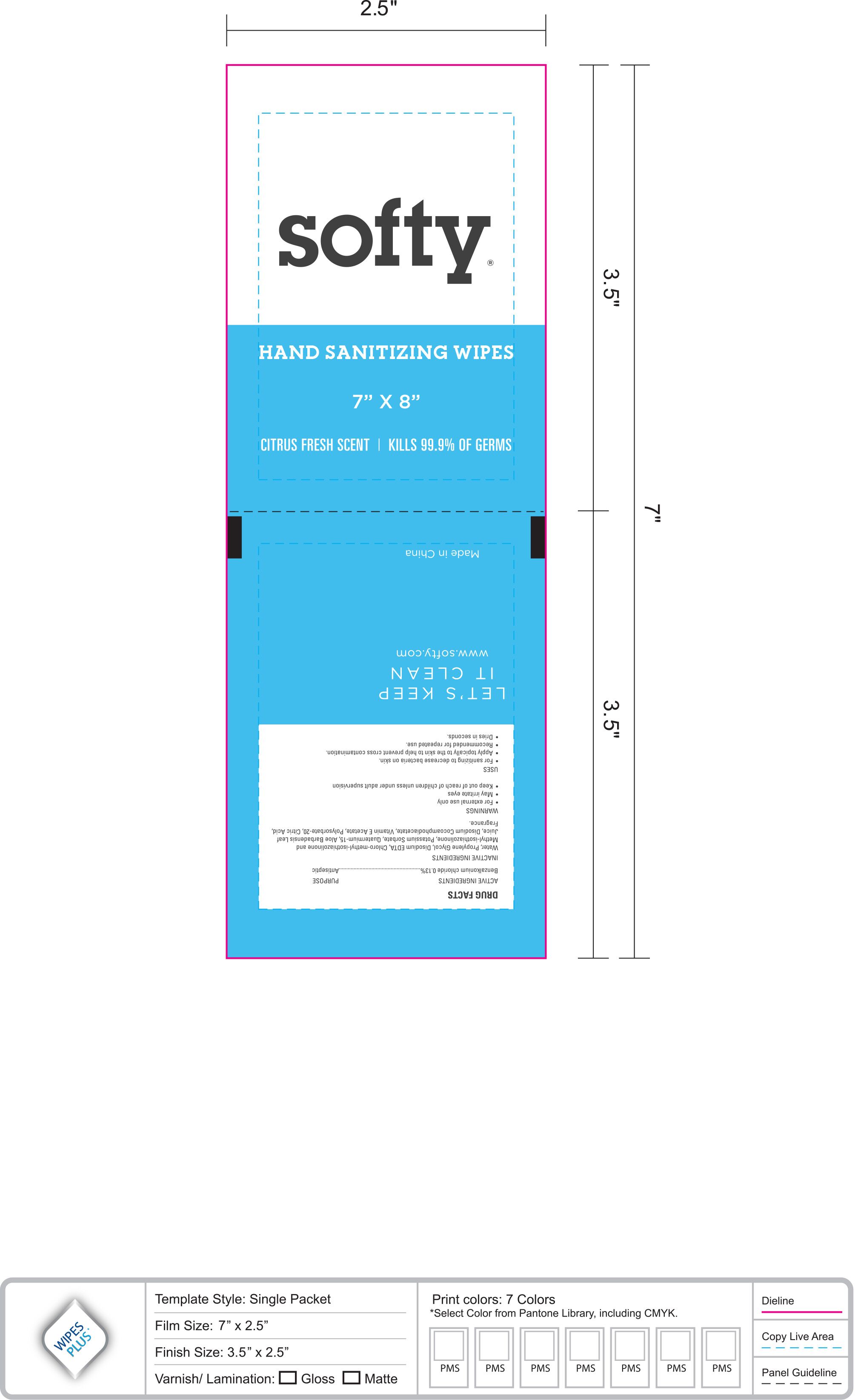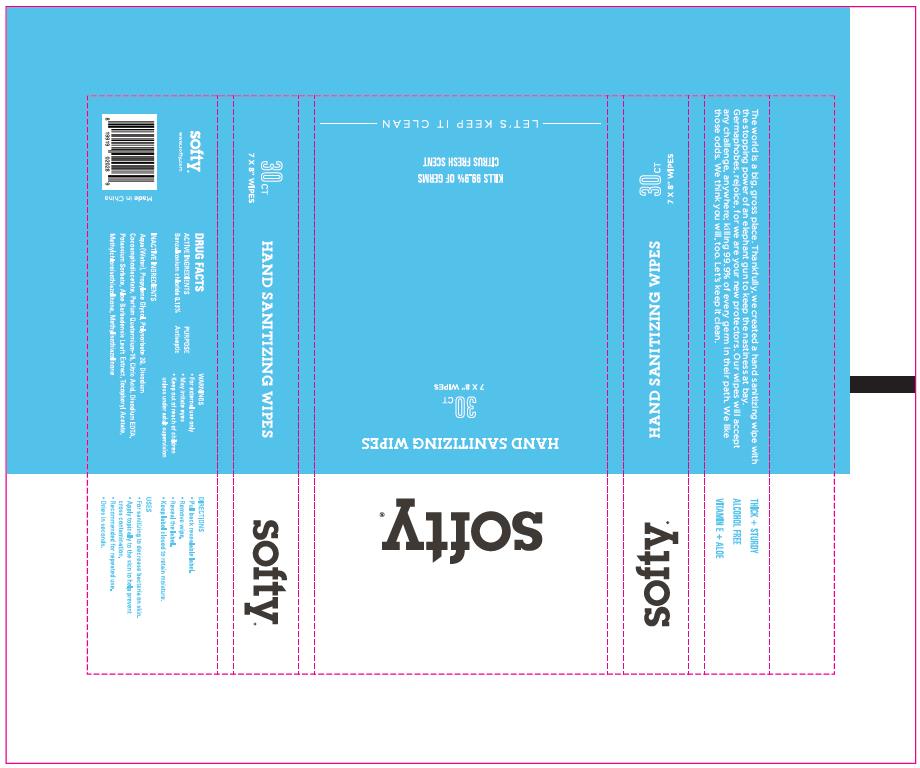 DRUG LABEL: HAND SANITIZING WIPES
NDC: 77046-100 | Form: PATCH
Manufacturer: ZheJiang HuaShun Technology Co.,Ltd
Category: otc | Type: HUMAN OTC DRUG LABEL
Date: 20200927

ACTIVE INGREDIENTS: METHYLCHLOROISOTHIAZOLINONE 0.0009 g/100 g; METHYLISOTHIAZOLINONE 0.0003 g/100 g; BRONOPOL 0.03 g/100 g; BENZALKONIUM CHLORIDE 0.13 g/100 g
INACTIVE INGREDIENTS: POTASSIUM SORBATE 0.02 g/100 g; PROPYLENE GLYCOL 0.5 g/100 g; POLYSORBATE 20 0.15 g/100 g; DISODIUM COCOAMPHODIACETATE 0.15 g/100 g; ALOE VERA LEAF 0.2 g/100 g; EDETATE DISODIUM 0.05 g/100 g; .ALPHA.-TOCOPHEROL ACETATE 0.01 g/100 g; CITRIC ACID MONOHYDRATE 0.02 g/100 g; WATER 98.7 g/100 g

Active Ingredient(s)

Benzalkonium chloride 0.13%. Purpose: Antiseptic

Purpose

Antiseptic

USES

For sanitizing to decrease bacteria on skin

apply topically to the skin to help prevent cross contamination

recommended for repeated use

dries in seconds

Warnings

For external use only.

May irritate eyes

Keep out of reach of children unless under adult supervision

Keep out of reach of children unless under adult supervision

Inactive ingredients

Water, Propylene Glycol,Disodium EDTA,Chloro-methyl-isothiazolinone and Methyl-isothiazolinone,Potassium Sorbate,Quatermium-15,Aloe Barbadensis Leaf Juice,Disodium Cocoamphodiacetate,Vitamin E Acetate,Polysorbate-20,Citric Acid,Fragrance.